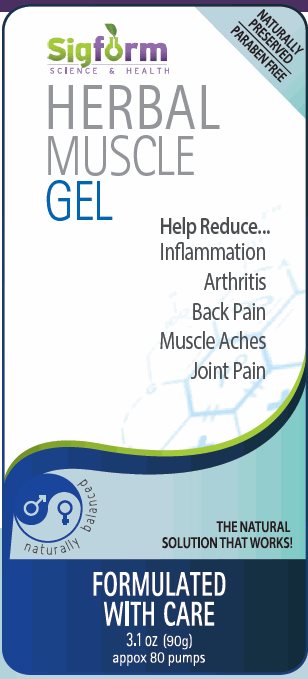 DRUG LABEL: Sigform Herbal Muscle
NDC: 69257-212 | Form: GEL
Manufacturer: Signature Formulations LLC
Category: otc | Type: HUMAN OTC DRUG LABEL
Date: 20150402

ACTIVE INGREDIENTS: MENTHOL 6 g/100 mL; CAMPHOR (SYNTHETIC) 2 g/100 mL
INACTIVE INGREDIENTS: WATER; DIMETHYL SULFONE; EUCALYPTUS OIL; PEPPERMINT OIL; CLOVE OIL; PHENOXYETHANOL; CARBOMER INTERPOLYMER TYPE A (ALLYL SUCROSE CROSSLINKED); METHYL SALICYLATE; SODIUM BICARBONATE; POTASSIUM SORBATE

Sigform Science & Health Herbal Muscle Gel

Active ingredient

Menthol USP 6%
Camphor 2%

Purpose

Pain Relief

Other ingredients

Purified Signature Water™, Methylsufonylmethane, Lubragel Np, Menthol crystals, Eucaliptus oil, Camphor powder, Peppermint oil, Clove Bud oil, Phenoxyethanol, Carbopol ultrez 10, Sweet Birch oil, Sodium bicarbonate, Potassium Sorbate.

Uses

For the temporary relief of minor aches and pains at muscles and joints associated with sore muscles, strains, joint discomfort & arthritis.

Warnings

Discontinue use if irritation or red skin develops, and consult a physician. Application is intended for external cosmetic use only. Consult a health care professional before using this or any product during pregnancy or while breastfeeding. Do not use around the eye area. Do not use if tamper-evident seal is broken or missing. Store in cool dry place.

These statements have not been evaluated by the food and drug administration. This product is not intended to treat, cure or prevent any disease.

Directions

Adults and children over 12 years. Massage into neck and shoulders to help relieve tension and stress. Rub into temples to help with headaches, and chest to relieve cold and flu. Apply prior to a workout or sports activity.

Manufactured in a FDA registered facility by

Signature Formulations LLC.
Phoenix, AZ

Package/Label Principal Display Panel

Sigform
SCIENCE & HEALTH

NATURALLY
PRESERVED
PARABEN FREE

HERBAL
MUSCLE
GEL

Help Reduce…
Inflammation
Arthritis
Back Pain
Muscle Aches
Joint Pain

naturally balanced

THE NATURAL
SOLUTION THAT WORKS!

FORMULATED
WITH CARE

3.1 oz (90g)
approx 80 pumps

Carton Label